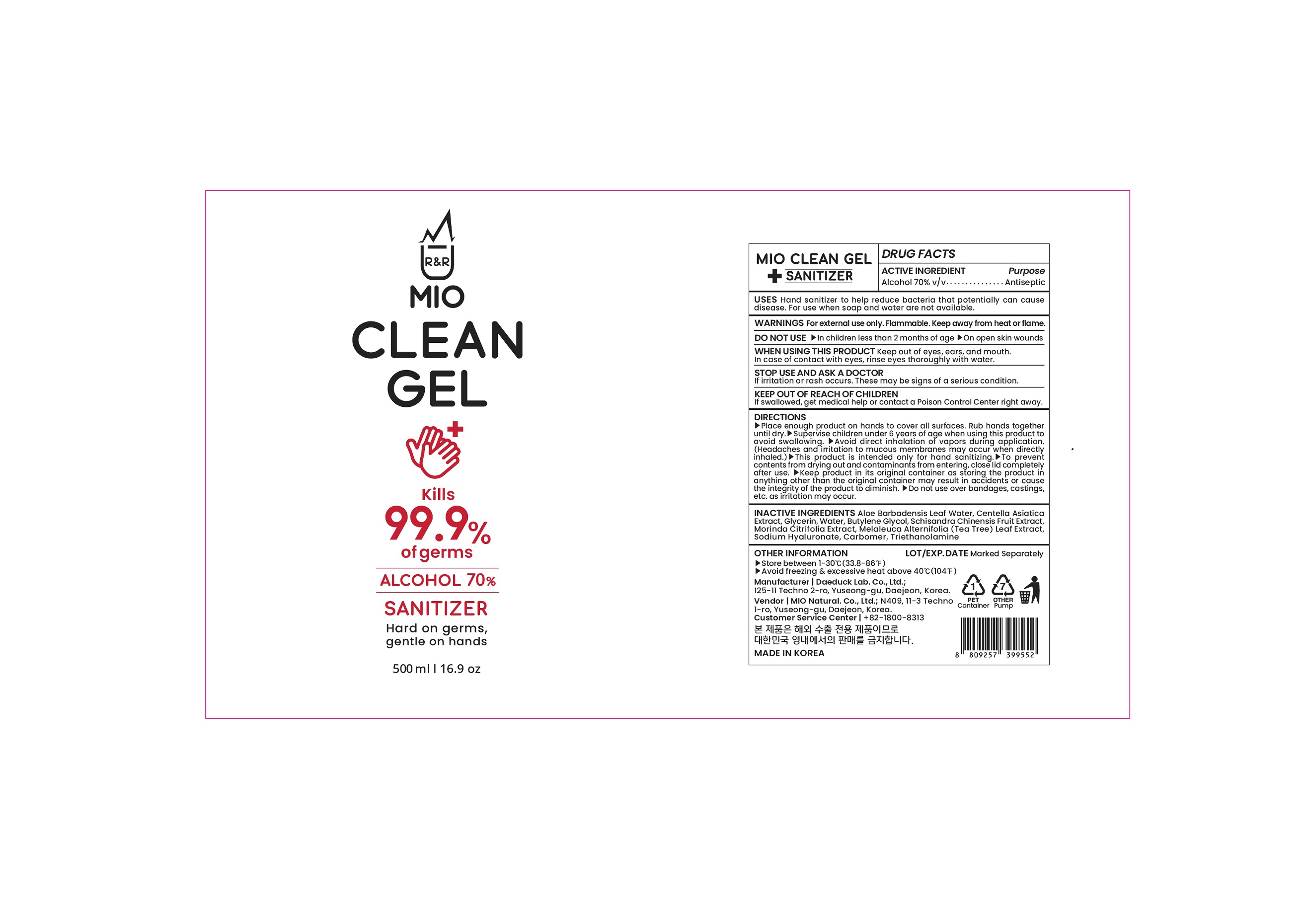 DRUG LABEL: MIO CLEAN gel
NDC: 76871-0001 | Form: GEL
Manufacturer: MiO Natural Co Ltd
Category: otc | Type: HUMAN OTC DRUG LABEL
Date: 20200829

ACTIVE INGREDIENTS: ALCOHOL 70 mL/100 mL
INACTIVE INGREDIENTS: GREEN TEA LEAF; GLYCERIN; HYALURONATE SODIUM; ALOE VERA LEAF; CARBOMER 940; TROLAMINE; WATER

Drug Facts

ACTIVE INGREDIENT

alcohol

INACTIVE INGREDIENT

aloe vera extract, centella asiatica extract, glycerin, water, butylene glycol, schisandra chinensis fruit extract, morinda citrifolia extract, melaleuca alternifolia leaf extract, sodium hyaluronate, carbomer, triethanolamine

PURPOSE

Sterilization of hands and skin

KEEP OUT OF REACH OF THE CHILDREN

INDICATIONS AND USAGE

Apply to clean, dry hands. Apply sufficient amount to thoroughly wet all surfaces of hands and fingers. Rub onto hands until dry.

Supervise children in the use of this product.

WARNINGS

■ Flammable. Keep away from fire or flame.

■ For external use only.

■ Do not use in eyes.

■ lf swallowed, get medical help promptly.

■ Stop use, ask doctor lf irritation occurs.

■ Keep out of reach of children.

DOSAGE AND ADMINISTRATION

for external use only